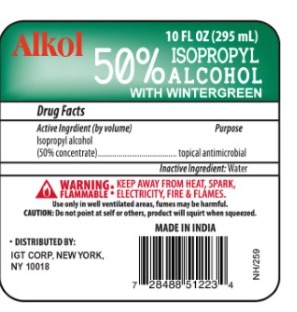 DRUG LABEL: RUBBING ALCOHOL
NDC: 78440-008 | Form: LIQUID
Manufacturer: INTERNATIONAL GENERAL TRADING CORP
Category: otc | Type: HUMAN OTC DRUG LABEL
Date: 20210312

ACTIVE INGREDIENTS: ALCOHOL 50 mL/100 mL
INACTIVE INGREDIENTS: WATER

ISOPROPYL ALCOHOL

Active Ingredient(s)

Isopropyl 50% concentrator

Purpose

Antiseptic, Hand Sanitizer

Use

To decrease germs in minor cuts and scrapes

Warnings

flammable, keep away from fire and flame

will produce serious gastric disturbance

Do not use

If allergic reactions

When using this product keep out of eyes, ears, and mouth. In case of contact with eyes, rinse eyes thoroughly with water.
Stop use and ask a doctor if irritation or rash occurs. These may be signs of a serious condition.
Keep out of reach of children. If swallowed, get medical help or contact a Poison Control Center right away.

Stop use and ask a doctor if irritation or rash occurs. These may be signs of a serious condition.

Keep out of reach of children. If swallowed, get medical help or contact a Poison Control Center right away.

Directions

- Place enough product on hands to cover all surfaces. Rub hands together until dry.
- Supervise children under 6 years of age when using this product to avoid swallowing.

Inactive ingredients

water

Other information

- Store between 15-30C (59-86F)
- Avoid freezing and excessive heat above 40C (104F)

Package Label - Principal Display Panel

295 ml

10 onz